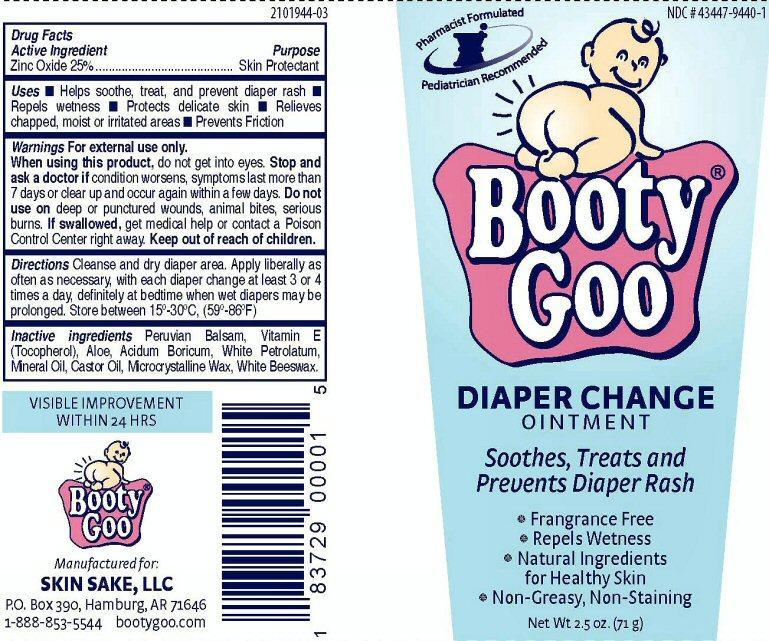 DRUG LABEL: Booty Goo
NDC: 43447-9440 | Form: OINTMENT
Manufacturer: Skin Sake, LLC
Category: otc | Type: HUMAN OTC DRUG LABEL
Date: 20130514

ACTIVE INGREDIENTS: ZINC OXIDE 17.75 g/71 g
INACTIVE INGREDIENTS: BALSAM PERU; .ALPHA.-TOCOPHEROL; ALOE; BORIC ACID; PETROLATUM; MINERAL OIL; CASTOR OIL; MICROCRYSTALLINE WAX; WHITE WAX

Active Ingredient

Drug Facts

Active Ingredient

Zinc Oxide 25%

Purpose

Skin Protectant

Keep out of reach of children

Uses

- Helps soothe, treat , and prevent diaper rash
- Repels wetness
- Protects delicate skin
- Relieves chapped, moist or irritated areas
- Prevents Friction

Warnings

For external use only.

When using this product, do not get into eyes.

Stop and ask a doctor if condition worsens, symptoms last more than 7 days or clear up and occur again within a few days.

Do not use on deep puncture wounds, animal bites, serious burns.

If swallowed, get medical help or contact a Poison control Center right away.

Directions

Cleanse and dry diaper area. Apply liberally as often as necessary, with each diaper change at least 3 or 4 times a day, definitely at bedtime when wet diapers may be prolonged. Store between 15° - 30° C, (59° - 86° F)

Inactive ingredients

Peruvian Balsam, Vitamin E (Tocopherol), Aloe, Acidum Boricum, White Petrolatum, Mineral Oil, Castor Oil, Microcrystalline Wax, White Beeswax.

Product Label

NDC # 434479440-1

Pharmacist Formulated Pediatrician Recommended

Booty®Goo

DIAPER CHANGE OINTMENT

Soothes, treats and prevents Diaper Rash

Frangrance Free
Repels Wetness
Natural Ingredients for Healthy Skin
Non-Greasey, Non-Staining

Net Wt 2.5 oz (71g)

VISIBLE IMPROVEMENT WITHIN 24 HRS

Manufactured by:

SKIN SAKE, LLC

P.O. Box 390, Hamburg, AT 71646

1-888-853-5544 bootygoo.com

2101944-03